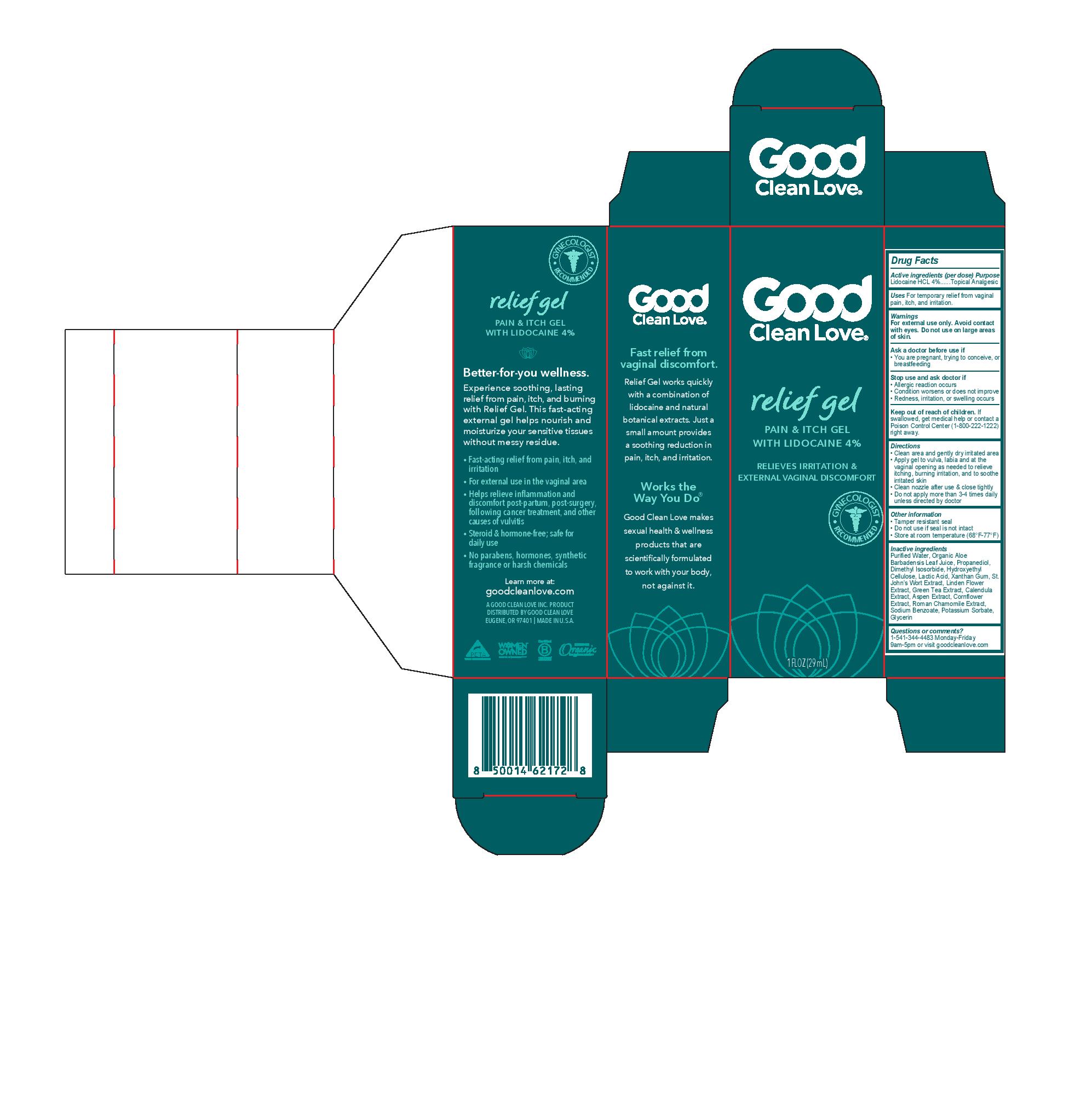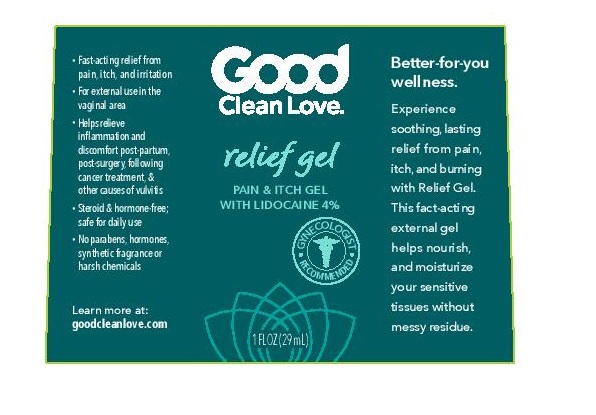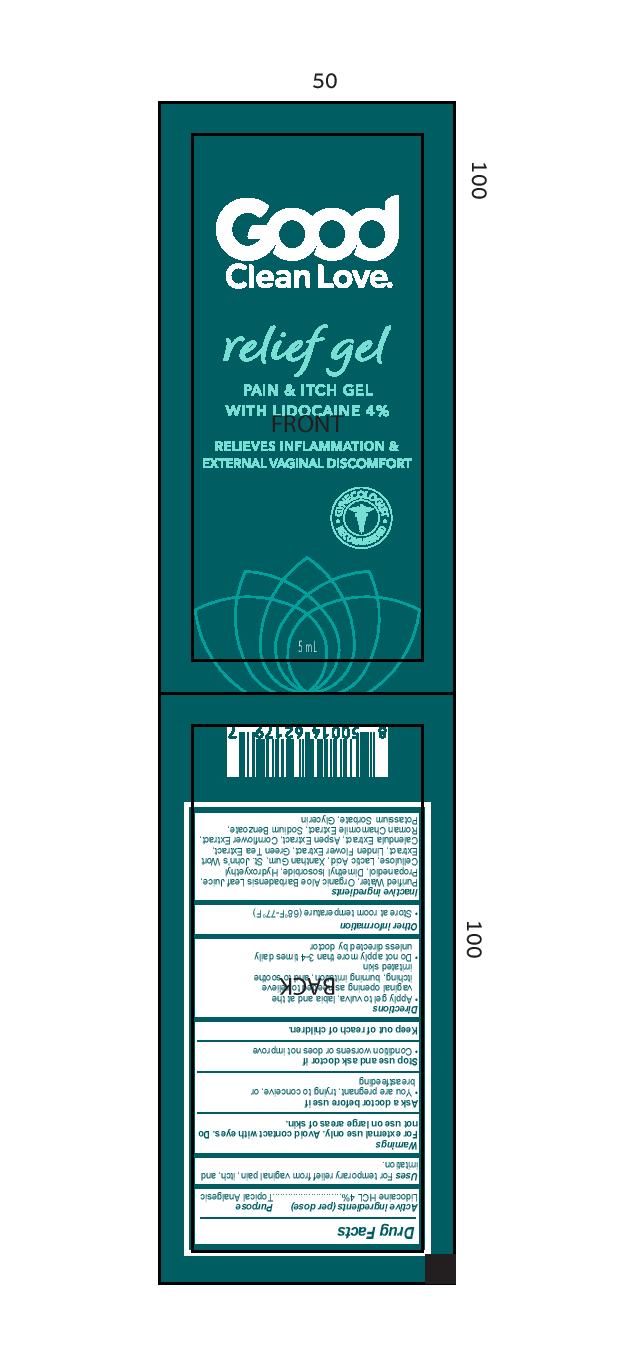 DRUG LABEL: Relief Gel
NDC: 73716-003 | Form: GEL
Manufacturer: Good Clean Love, Inc.
Category: otc | Type: HUMAN OTC DRUG LABEL
Date: 20250707

ACTIVE INGREDIENTS: LIDOCAINE HYDROCHLORIDE 4 g/100 mL
INACTIVE INGREDIENTS: SODIUM BENZOATE; POTASSIUM SORBATE; GLYCERIN; WATER; ALOE VERA LEAF; PROPANEDIOL; DIMETHYL ISOSORBIDE; ST. JOHN'S WORT; GREEN TEA LEAF; CALENDULA OFFICINALIS FLOWER; TILIA CORDATA FLOWER; POPULUS TREMULOIDES BARK; HYDROXYETHYL CELLULOSE, UNSPECIFIED; LACTIC ACID; XANTHAN GUM; CENTAUREA CYANUS FLOWER; CHAMAEMELUM NOBILE FLOWER

Relief Gel

Active ingredients (per dose)

Lidocaine HCL 4%

Purpose

Lidocaine HCL 4%................Topical Analgesic

Uses

For temporary relief from vaginal pain, itch, and irritation

Warnings

For external use only. Avoid contact with eyes. Do not use on large areas of skin.

Ask a doctor before use if

- You are pregnant, trying to conceive, or breastfeeding

Stop use and ask doctor if

- Allergic reaction occurs
- Condition worsens or does not improve
- Redness, irritation, or swelling occurs

Keep out of reach of children.If swallowed, get medical help or contact a Poison Control Center (1-800-222-1222) right away.

Directions

- Clean area and gently dry irritated area
- Apply gel to vulva, labia and at the vaginal opening as needed to relieve itching, burning irritation, and to soothe irritated skin
- Clean nozzle after use & close tightly
- Do not apply more than 3-4 times daily unless directed by doctor

Other information

- Tamper resistant seal
- Do not use if seal is not intact
- Store at room temperature (68F-77F)

Inactive ingredients

Purified Water, Organic Aloe Barbadensis Leaf Juice, Propanediol, Dimethyl Isosorbide, Hydroxyethyl Cellulose, Lactic Acid, Xanthan Gum, St. John’s Wort Extract, Linden Flower Extract, Green Tea Extract, Calendula Extract, Aspen Extract, Cornflower Extract, Roman Chamomile Extract, Sodium Benzoate, Potassium Sorbate, Glycerin

Questions or comments?

1-541-344-4483 Monday-Friday

9am-5pm or visit goodcleanlove.com

PACKAGE LABEL

Good Clean Love

relief gel

Pain & Itch Gel

With Lidocaine 4%

Relieves irritation & external vaginal discomfort

Gynecologist Recommended

1 Fl Oz (29mL)